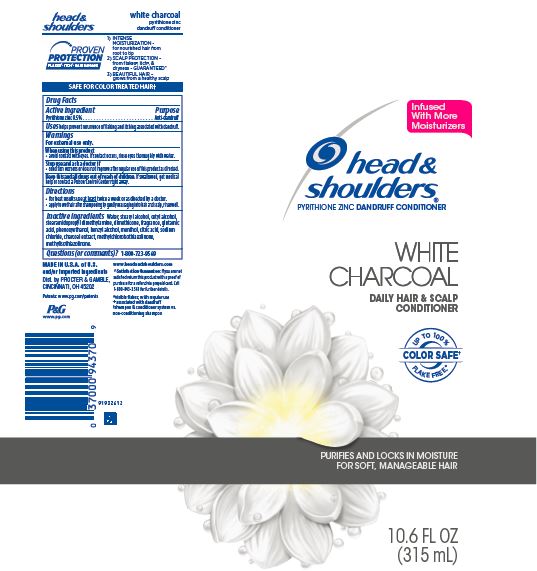 DRUG LABEL: Head and Shoulders White Charcoal Daily Hair and Scalp Conditioner
NDC: 69423-279 | Form: LOTION
Manufacturer: The Procter & Gamble Manufacturing Company
Category: otc | Type: HUMAN OTC DRUG LABEL
Date: 20260128

ACTIVE INGREDIENTS: PYRITHIONE ZINC 0.5 g/100 mL
INACTIVE INGREDIENTS: METHYLCHLOROISOTHIAZOLINONE; METHYLISOTHIAZOLINONE; MENTHOL; ACTIVATED CHARCOAL; BLUE 1; WATER; STEARYL ALCOHOL; CETYL ALCOHOL; GLUTAMIC ACID; DIMETHICONE; PHENOXYETHANOL; BENZYL ALCOHOL; CITRIC ACID; SODIUM CHLORIDE

Head and Shoulders® White Charcoal Daily Haiir and Scalp Conditioner

Drug Facts

Active ingredient

Pyrithione zinc 0.5%

Purpose

Anti-dandruff

Uses

helps prevent recurrence of flaking and itching associated with dandruff.

Warnings

For external use only.

When using this product

- avoid contact with eyes. If contact occurs, rinse eyes thoroughly with water.

Stop use and ask a doctor if

- condition worsens or does not improve after regular use of this product as directed.

KEEP OUT OF REACH OF CHILDREN

Keep this and all drugs out of reach of children. If swallowed, get medical help or contact a Poison Control Center right away.

Directions

- for best results use at least twice a week or as directed by a doctor.
- apply to wet hair after shampooing by gently massaging into hair and scalp, rinse well.

Inactive ingredients

Water, stearyl alcohol, cetyl alcohol, stearamidopropyl dimethylamine, dimethicone, fragrance, glutamic acid, phenoxyethanol, benzyl alcohol, menthol, citric acid, sodium chloride, charcoal extract, methylchloroisothiazolinone, methylisothiazolinone.

Questions (or comments)?

1-800-723-9569

Dist. by PROCTER & GAMBLE,
CINCINNATI, OH 45202

PRINCIPAL DISPLAY PANEL - 315 mL TubeLabel

head &
shoulders®
pyrithione zinc dandruff conditioner

WHITE CHARCOAL

DAILY HAIR & SCALP

CONDITIONER

PURIFIES AND LOCKS IN MOISTURE

FOR SOFT, MANAGEABLE HAIR

10.6 FL OZ (315 mL)